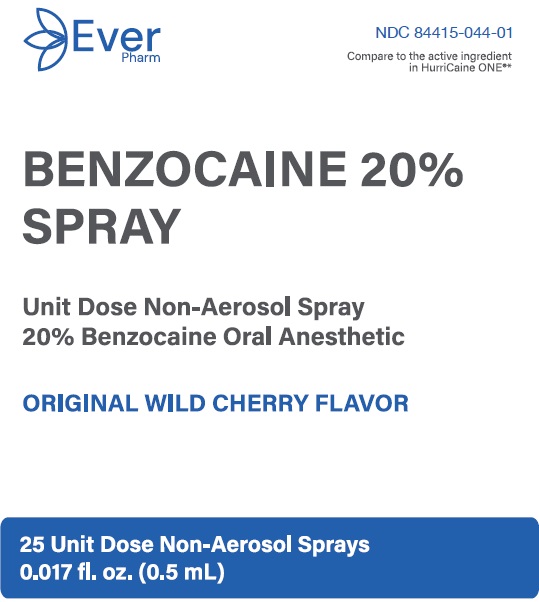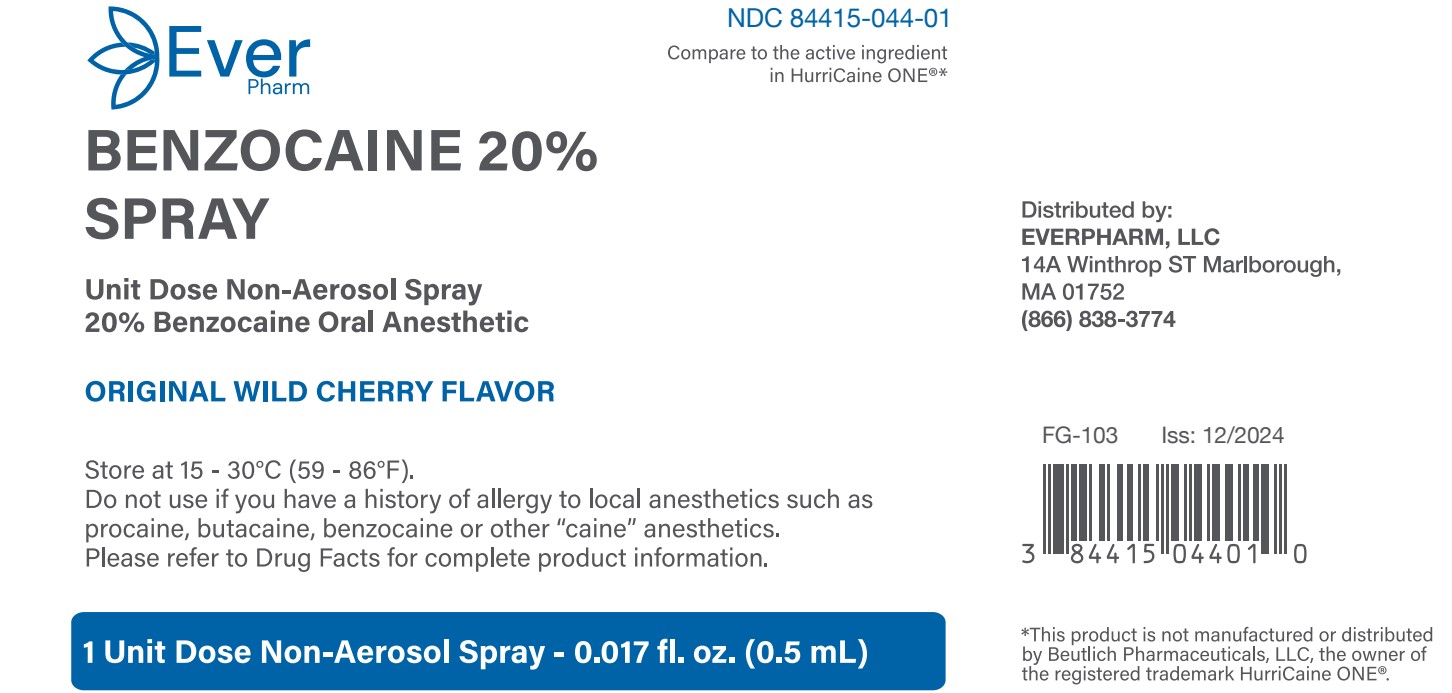 DRUG LABEL: Benzocaine
NDC: 84415-044 | Form: SPRAY
Manufacturer: Everpharm LLC
Category: otc | Type: HUMAN OTC DRUG LABEL
Date: 20250115

ACTIVE INGREDIENTS: BENZOCAINE 200 mg/1 mL
INACTIVE INGREDIENTS: POLYETHYLENE GLYCOL 400; SUCRALOSE; CHERRY

Benzocaine 20% Spray

Active Ingredient

Benzocaine 20%

Purpose

Oral Anesthetic

INDICATIONS AND USAGE

Usesfor the temporary relief of occasional minor irritation and pain associated with sore mouth and throat

Warnings

Methemoglobinemia warning:Use of this product may cause methemoglobinemia, a serious condition that must be treated promptly because it reduces the amount of oxygen carried in blood. This can occur even if you have used this product before. Stop use and seek immediate medical attention if you or a child in your care develops:
• pale, gray, or blue colored skin (cyanosis)
• headache
• rapid heart rate
• shortness of breath
• dizziness or lightheadedness
• fatigue or lack of energy

Allergy alert:Do not use if you have a history of allergy to local anesthetics such as procaine, butacaine, benzocaine or other "caine" anesthetics.

Sore throat warning:if sore throat is severe, persists for more than 2 days, is accompanied or followed by fever, headache, rash, swelling, nausea, or vomiting, consult a doctor promptly. If sore mouth symptoms do not improve in 7 days, or irritation, pain, or redness persists or worsens, see your dentist or doctor promptly.

Do not use

- if foil pouch has been previously opened
- for teething
- in children under 2 years of age

When using this product

- avoid contact with eyes

Keep out of reach of children.

If more than used for pain is accidently swallowed, get medical help or contact a Poison Control Center (1-800-222-1222) Immediately

Directions

- do not exceed recommended dosage

adults and children 2 years of age and older: use up to 4 times daily or as directed by a dentist or doctor

children under 12 years of age: should be supervised in the use of the product

children under 2 years of age: do not use

Other information

- store at 15-30 °C (59-86 °F)

Inactive ingredients

cherry flavor, polyethylene glycol, sucralose

Questions or comments?

(855) 879-4368

Principal Display Panel

EverPharm

NDC 84415-044-01

Benzocaine 20% Spray

Unit Dose Non-Aerosol Spray

20% Benzocaine Oral Anesthetic

25 Unit Dose Non-Aerosol Sprays

0.017 fl.oz. (0.5 mL)

Principal Display Panel

EverPharm

NDC 84415-044-01

Benzocaine 20% Spray

Unit Dose Non-Aerosol Spray

20% Benzocaine Oral Anesthetic

1 Unit Dose Non-Aerosol Spray

0.017 fl.oz. (0.5 mL)